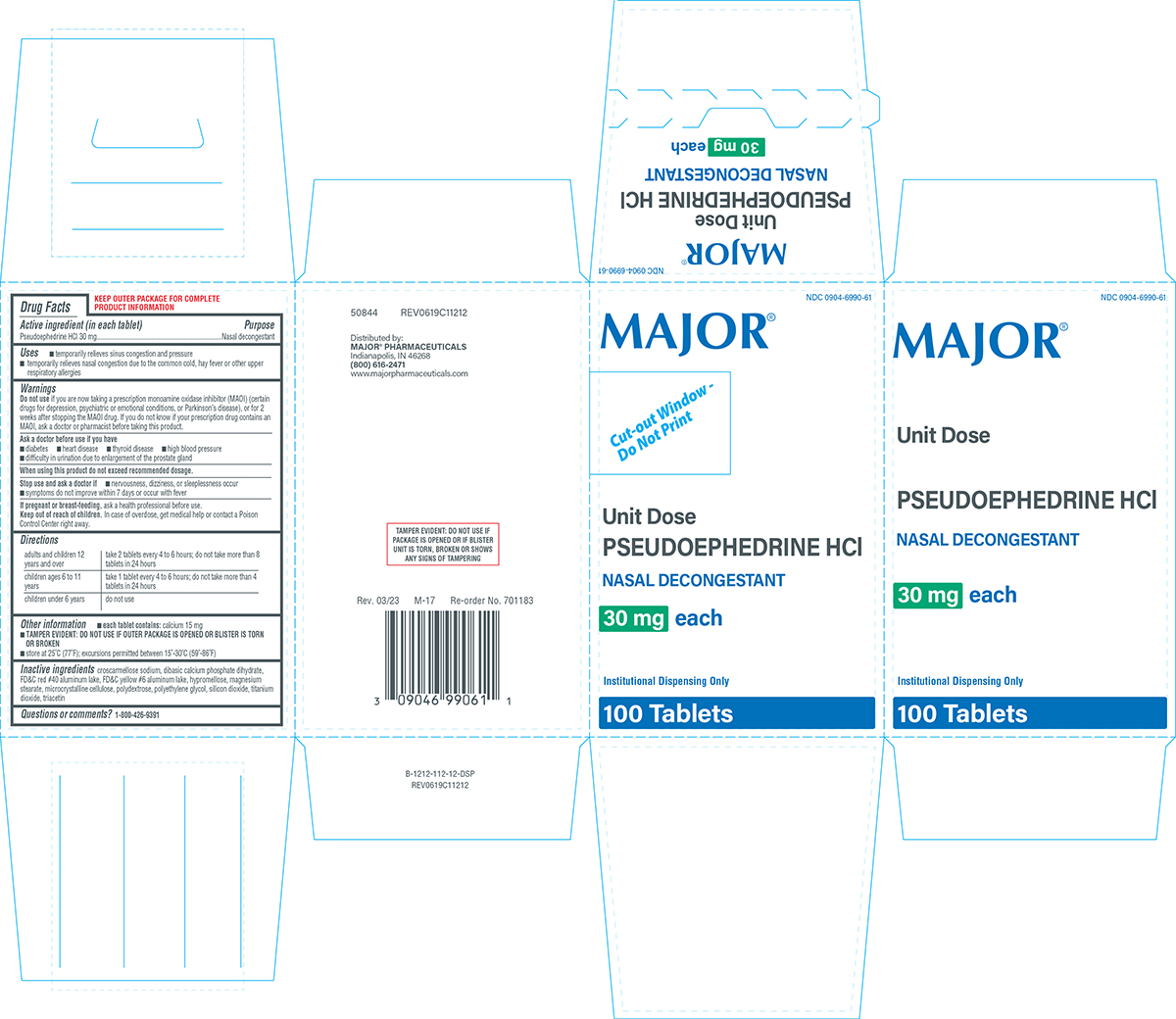 DRUG LABEL: Pseudoephedrine HCl
NDC: 0904-6990 | Form: TABLET, FILM COATED
Manufacturer: Major Pharmaceuticals
Category: otc | Type: HUMAN OTC DRUG LABEL
Date: 20260205

ACTIVE INGREDIENTS: PSEUDOEPHEDRINE HYDROCHLORIDE 30 mg/1 1
INACTIVE INGREDIENTS: CROSCARMELLOSE SODIUM; DIBASIC CALCIUM PHOSPHATE DIHYDRATE; FD&C RED NO. 40 ALUMINUM LAKE; FD&C YELLOW NO. 6 ALUMINUM LAKE; HYPROMELLOSE, UNSPECIFIED; MAGNESIUM STEARATE; MICROCRYSTALLINE CELLULOSE; POLYDEXTROSE; POLYETHYLENE GLYCOL, UNSPECIFIED; SILICON DIOXIDE; TITANIUM DIOXIDE; TRIACETIN

Major 44-112-DSP

Active ingredient (in each tablet)

Pseudoephedrine HCl 30 mg

Purpose

Nasal decongestant

Uses

- temporarily relieves sinus congestion and pressure
- temporarily relieves nasal congestion due to the common cold, hay fever or other upper respiratory allergies

Warnings

Do not use

if you are now taking a prescription monoamine oxidase inhibitor (MAOI) (certain drugs for depression, psychiatric or emotional conditions, or Parkinson’s disease), or for 2 weeks after stopping the MAOI drug. If you do not know if your prescription drug contains an MAOI, ask a doctor or pharmacist before taking this product.

Ask a doctor before use if you have

- diabetes
- heart disease
- thyroid disease
- high blood pressure
- difficulty in urination due to enlargement of the prostate gland

When using this product

do not exceed recommended dosage.

Stop use and ask a doctor if

- nervousness, dizziness, or sleeplessness occur
- symptoms do not improve within 7 days or occur with fever

If pregnant or breast-feeding,

ask a health professional before use.

Keep out of reach of children.

In case of overdose, get medical help or contact a Poison Control Center right away.

Directions

adults and children 12 years and over | take 2 tablets every 4 to 6 hours; do not take more than 8 tablets in 24 hours
children ages 6 to 11 years | take 1 tablet every 4 to 6 hours; do not take more than 4 tablets in 24 hours
children under 6 years | do not use

Other information

- each tablet contains: calcium 15 mg
- TAMPER EVIDENT: DO NOT USE IF OUTER PACKAGE IS OPENED OR BLISTER IS TORN OR BROKEN
- store at 25°C (77°F); excursions permitted between 15°-30°C (59°-86°F)

Inactive ingredients

croscarmellose sodium, dibasic calcium phosphate dihydrate, FD&C red #40 aluminum lake, FD&C yellow #6 aluminum lake, hypromellose, magnesium stearate, microcrystalline cellulose, polydextrose, polyethylene glycol, silicon dioxide, titanium dioxide, triacetin

Questions or comments?

1-800-426-9391

Principal Display Panel

MAJOR®

NDC 0904-6990-61

Unit Dose

PSEUDOEPHEDRINE HCI

NASAL DECONGESTANT

30 mg each

Institutional Dispensing only

100 TABLETS

TAMPER EVIDENT: DO NOT USE IF
PACKAGE IS OPENED OR IF BLISTER
UNIT IS TORN, BROKEN OR SHOWS
ANY SIGNS OF TAMPERING

50844 REV0619C11212

Distributed by:
MAJOR® PHARMACEUTICALS
Indianapolis, IN 46268
(800) 616-2471
www.majorpharmaceuticals.com

Rev. 03/23 M-17 Re-order No. 701183

Major 44-112